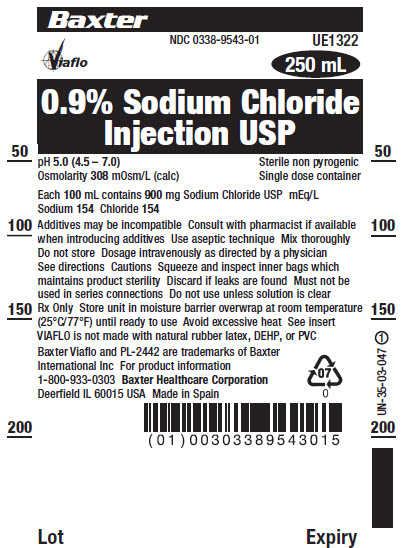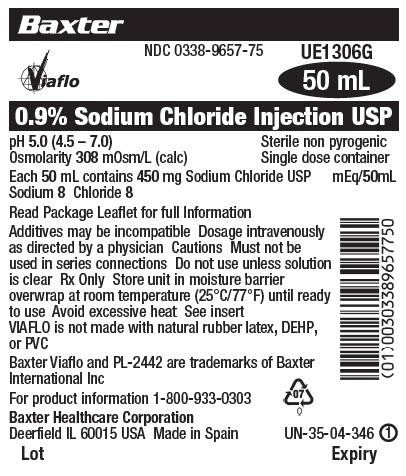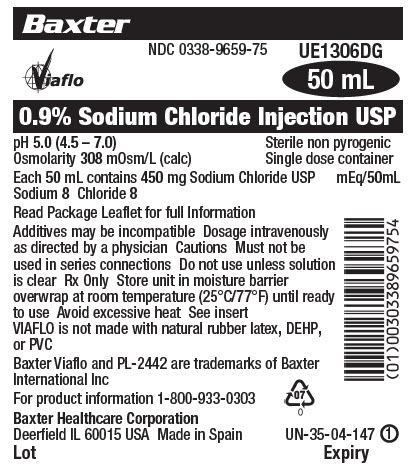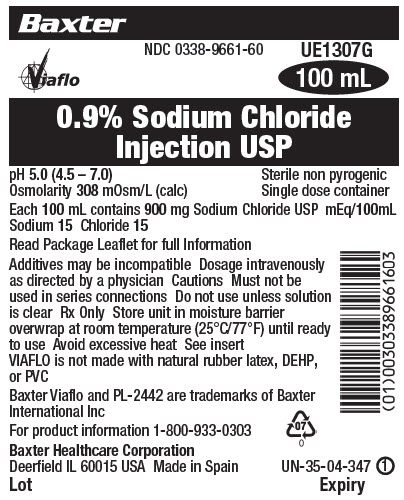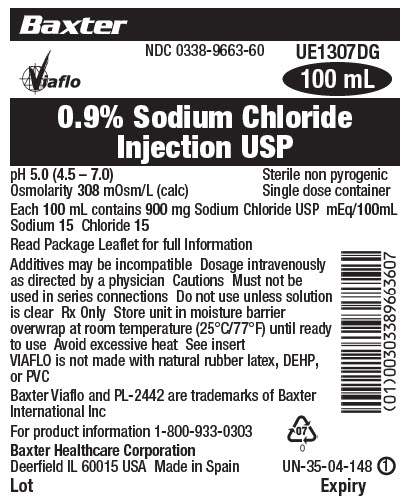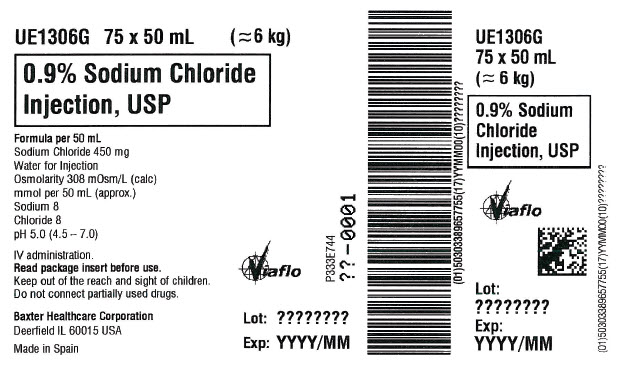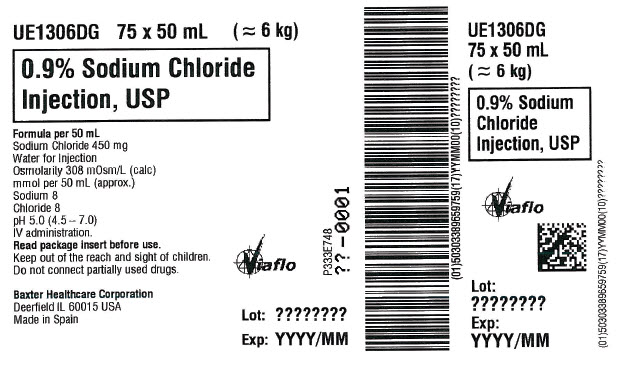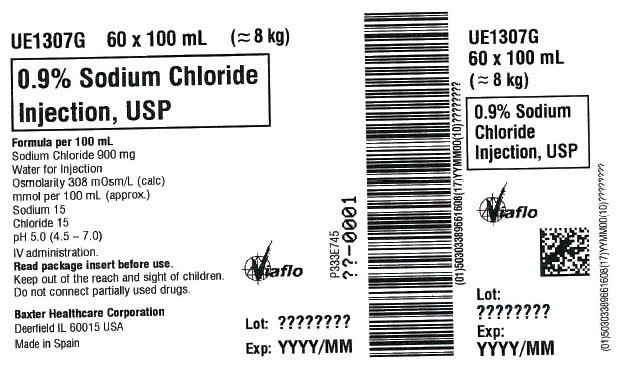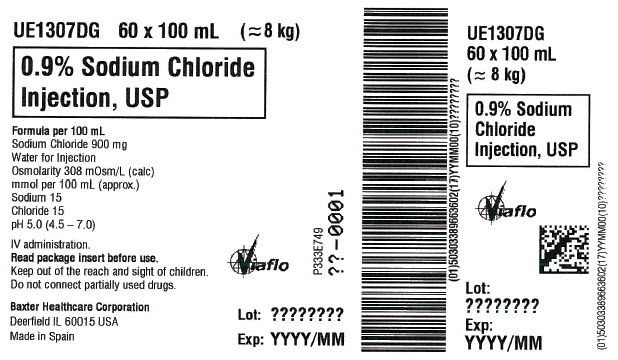 DRUG LABEL: SODIUM CHLORIDE
NDC: 0338-9543 | Form: INJECTION, SOLUTION
Manufacturer: Baxter Healthcare Corporation
Category: prescription | Type: HUMAN PRESCRIPTION DRUG LABEL
Date: 20240809

ACTIVE INGREDIENTS: SODIUM CHLORIDE 9 g/1000 mL
INACTIVE INGREDIENTS: WATER

Sodium Chloride Injection, USP
in VIAFLO Plastic Container

DESCRIPTION

Sodium Chloride Injection, USP is a sterile, nonpyrogenic solution for fluid and electrolyte replenishment in single dose containers for intravenous administration. It contains no antimicrobial agents. The nominal pH is 5.0 (4.5 to 7.0). Composition, osmolarity, and ionic concentration are shown below:

0.9% Sodium Chloride Injection, USP contains 9 g/L Sodium Chloride, USP (NaCl) with an osmolarity of 308 mOsmol/L (calc). It contains 154 mEq/L sodium and 154 mEq/L chloride.

VIAFLO is a flexible plastic container fabricated from a multilayer sheeting (PL-2442) composed of Polypropylene (PP), Polyamide (PA) and Polyethylene (PE). The amount of water that can permeate from inside the container into the overwrap is insufficient to affect the solution significantly. Two different administration connectors are available with VIAFLO containers. The VIAFLO dripless access container (DAC) will not drip once the spike is removed. The non-DAC VIAFLO will drip once the spike is removed from the administration port.

VIAFLO is not made with natural rubber latex, DEHP, or PVC.

CLINICAL PHARMACOLOGY

Sodium Chloride Injection, USP has value as a source of water and electrolytes. It is capable of inducing diuresis depending on the clinical condition of the patient.

INDICATIONS AND USAGE

Sodium Chloride Injection, USP is indicated as a source of water and electrolytes.

0.9% Sodium Chloride Injection, USP is also indicated for use as a priming solution in hemodialysis procedures.

CONTRAINDICATIONS

None known.

WARNINGS

Hypersensitivity

Hypersensitivity and infusion reactions, including hypotension, pyrexia, tremor, chills, urticaria, rash, and pruritus have been reported with 0.9% Sodium Chloride Injection, USP.

Stop the infusion immediately if signs or symptoms of a hypersensitivity reaction develop, such as tachycardia, chest pain, dyspnea and flushing. Appropriate therapeutic countermeasures must be instituted as clinically indicated.

Electrolyte Imbalances

Fluid Overload

Depending on the volume and rate of infusion, and the patient’s underlying clinical condition, the intravenous administration of Sodium Chloride Injection, USP can cause fluid disturbances such as overhydration/hypervolemia and congested states, including pulmonary congestion and edema.

Avoid 0.9% Sodium Chloride Injection, USP in patients with or at risk for fluid and/or solute overloading. If use cannot be avoided, monitor fluid balance, electrolyte concentrations, and acid base balance, as needed and especially during prolonged use.

Hyponatremia

Sodium Chloride Injection, USP may cause hyponatremia. Hyponatremia can lead to acute hyponatremic encephalopathy characterized by headache, nausea, seizures, lethargy, and vomiting. Patients with brain edema are at particular risk of severe, irreversible and life-threatening brain injury.

The risk of hospital-acquired hyponatremia is increased in patients with cardiac or pulmonary failure, and in patients with non-osmotic vasopressin release (including SIADH) treated with high volume of Sodium Chloride Injection, USP.

The risk for hyponatremia is increased in pediatric patients, elderly patients, postoperative patients, those with psychogenic polydipsia, and in patients treated with medications that increase the risk of hyponatremia (such as diuretics, certain antiepileptic and psychotropic medications). See DRUG INTERACTIONS.

Patients at increased risk for developing complications of hyponatremia such as hyponatremic encephalopathy, include pediatric patients, women (in particular pre-menopausal women), patients with hypoxemia, and patients with underlying central nervous system disease. Avoid Sodium Chloride Injection, USP in patients with or at risk for hyponatremia. If use cannot be avoided, monitor serum sodium concentrations.

Rapid correction of hyponatremia is potentially dangerous with risk of serious neurologic complications. Brain adaptations reducing risk of cerebral edema make the brain vulnerable to injury when chronic hyponatremia is too rapidly corrected, which is known as osmotic demyelination syndrome (ODS). To avoid complications, monitor serum sodium and chloride concentrations, fluid status, acid-base balance, and signs of neurologic complications.

Hypernatremia

Hypernatremia may occur with Sodium Chloride Injection, USP. Conditions that may increase the risk of hypernatremia, fluid overload and edema (central and peripheral), include patients with: primary hyperaldosteronism; secondary hyperaldosteronism associated with, for example, hypertension, congestive heart failure, liver disease (including cirrhosis), renal disease (including renal artery stenosis, nephrosclerosis); and pre-eclampsia.

Certain medications, such as corticosteroids or corticotropin, may also increase risk of sodium and fluid retention, see DRUG INTERACTIONS.

Avoid Sodium Chloride Injection, USP in patients with, or at risk for, hypernatremia. If use cannot be avoided, monitor serum sodium concentrations.

Rapid correction of hypernatremia is potentially dangerous with risk of serious neurologic complications. Excessively rapid correction of hypernatremia is also associated with a risk for serious neurologic complications such as osmotic demyelination syndrome (ODS) with risk of seizures and cerebral edema.

PRECAUTIONS

Patients with Severe Renal Impairment

Administration of Sodium Chloride Injection, USP in patients with or at risk of severe renal impairment, may result in hypernatremia and/or fluid overload (see WARNINGS). Avoid Sodium Chloride Injection, USP in patients with severe renal impairment or conditions that may cause sodium and/or potassium retention, fluid overload, or edema. If use cannot be avoided, monitor patients with severe renal impairment for development of these adverse reactions.

Drug Interactions

Other Products that Affect Fluid and/or Electrolyte Balance

Administration of Sodium Chloride Injection, USP to patients treated concomitantly with drugs associated with sodium and fluid retention may increase the risk of hypernatremia and volume overload. Avoid use of Sodium Chloride Injection, USP in patients receiving such products, such as corticosteroids or corticotropin. If use cannot be avoided, monitor serum electrolytes, fluid balance and acid base balance.

Lithium

Renal sodium and lithium clearance may be decreased during administration of Sodium Chloride Injection, USP. Monitor serum lithium concentration during concomitant use.

Renal sodium and lithium clearance may be increased during administration of 0.9% Sodium Chloride Injection, USP. Monitor serum lithium concentrations during concomitant use.

Other Drugs that Increase the Risk of Hyponatremia

Administration of Sodium Chloride Injection, USP in patients treated concomitantly with medications associated with hyponatremia may increase the risk of developing hyponatremia.

Avoid use of Sodium Chloride Injection, USP in patients receiving products, such as diuretics, and certain antiepileptic and psychotropic medications. Drugs that increase the vasopressin effect reduce renal electrolyte free water excretion and may also increase the risk of hyponatremia following treatment with intravenous fluids. If use cannot be avoided, monitor serum sodium concentrations.

Pregnancy

There are no adequate and well controlled studies with Sodium Chloride Injection, USP in pregnant women and animal reproduction studies have not been conducted with this drug. Therefore, it is not known whether Sodium Chloride Injection, USP can cause fetal harm when administered to a pregnant woman. Sodium Chloride Injection, USP should be given during pregnancy only if the potential benefit justifies the potential risk to the fetus.

Nursing Mothers

It is not known whether this drug is present in human milk. Because many drugs are present in human milk, caution should be exercised when Sodium Chloride Injection, USP is administered to a nursing woman.

Pediatric Use

The use of Sodium Chloride Injection, USP in pediatric patients is based on clinical practice. (See DOSAGE AND ADMINISTRATION).

Closely monitor plasma electrolyte concentrations in pediatric patients who may have impaired ability to regulate fluids and electrolytes. In very low birth weight infants, excessive or rapid administration of Sodium Chloride Injection, USP may result in increased serum osmolality and risk of intracerebral hemorrhage.

Children (including neonates and older children) are at increased risk of developing hyponatremia as well as for developing hyponatremic encephalopathy.

Geriatric Use

Geriatric patents are at increased risk of developing electrolyte imbalances. Sodium Chloride Injection, USP is known to be substantially excreted by the kidney, and the risk of toxic reactions to this drug may be greater in patients with impaired renal function. Therefore, dose selection for an elderly patient should be cautious, usually starting at the low end of the dosing range, reflecting the greater frequency of decreased hepatic, renal, or cardiac function, and of concomitant disease or other drug therapy. Consider monitoring renal function in elderly patients.

ADVERSE REACTIONS

Post-Marketing Adverse Reactions

The following adverse reactions have been identified during post approval use of Sodium Chloride Injection, USP. Because these reactions are reported voluntarily from a population of uncertain size, it is not always possible to reliably estimate their frequency or establish a causal relationship to drug exposure.

The following adverse reactions have been reported in the post-marketing experience during use of 0.9% Sodium Chloride Injection, USP and include the following:

General disorders and administration site conditions: Infusion site erythema, injection site streaking, burning sensation, and infusion site urticaria

Hypersensitivity reactions: Hypotension, pyrexia, tremor, chills, urticaria, rash, and pruritus.

Metabolism and nutrition disorders: Hypernatremia, hyponatremia, hyperchloremic metabolic acidosis.

Nervous System Disorders: Hyponatremic encephalopathy

If an adverse reaction does occur, discontinue the infusion, evaluate the patient, institute appropriate therapeutic countermeasures and save the remainder of the fluid for examination if deemed necessary.

OVERDOSAGE

Excessive administration of:

- 0.9% Sodium Chloride Injection, USP may lead to hypernatremia. Hypernatremia can lead to CNS manifestations, including seizures, coma, cerebral edema and death.
- Sodium Chloride Injection, USP can cause fluid overload (which can lead to pulmonary and/or peripheral edema). See WARNINGS and ADVERSE REACTIONS.

When assessing an overdose, any additives in the solution must also be considered. The effects of an overdose may require immediate medical attention and treatment.

Interventions include discontinuation of Sodium Chloride Injection, USP administration, dose reduction, and other measures as indicated for the specific clinical constellation (e.g., monitoring of fluid balance, electrolyte concentrations and acid base balance).

DOSAGE AND ADMINISTRATION

Important Administration Instructions

- Sodium Chloride Injection, USP is intended for intravenous administration using sterile equipment.
- Do not connect flexible plastic containers in series in order to avoid air embolism due to possible residual air contained in the primary container.
- Set the vent to the closed position on a vented intravenous administration set to prevent air embolism.
- Use a dedicated line without any connections to avoid air embolism.
- Do not pressurize intravenous solutions contained in flexible plastic containers to increase flow rates in order to avoid air embolism due to incomplete evacuation of residual air in the container.
- Prior to infusion, visually inspect the solution for particulate matter and discoloration. The solution should be clear and there should be no precipitates. Do not administer unless solution is clear, and container is undamaged.

Dosing Information

The choice of product, dosage, volume, rate, and duration of administration is dependent upon the age, weight and clinical condition of the patent and concomitant therapy, and administration should be determined by a physician experienced in intravenous fluid therapy.

Introduction of Additives

Additives may be incompatible.

Evaluate all additions to the plastic container for compatibility and stability of the resulting preparation. Consult with a pharmacist, if available.

If, in the informed judgment of the physician, it is deemed advisable to introduce additives, use aseptic technique. Mix thoroughly when additives have been introduced. After addition, if there is discoloration and/or the appearance of precipitates, insoluble complexes or crystals, do not use. Do not store solutions containing additives. Discard any unused portion.

HOW SUPPLIED

The available sizes of each 0.9% Sodium Chloride Injection, USP in VIAFLO dripless access containers (DAC) and non-DAC plastic containers are shown below. VIAFLO DAC will not drip once the spike is removed. VIAFLO non-DAC will drip once the spike is removed from the administration port:

Code | Size (mL) | Product | NDC
UE1306G | 50 | Non-DAC | 0338-9657-75
UE1306DG | 50 | DAC | 0338-9659-75
UE1307G | 100 | Non-DAC | 0338-9661-60
UE1307DG | 100 | DAC | 0338-9663-60
UE1322 | 250 | Non-DAC | 0338-9543-01
UE1322D | 250 | DAC | 0338-9543-02
UE1323 | 500 | Non-DAC | 0338-9543-03
UE1323D | 500 | DAC | 0338-9543-04
UE1324 | 1000 | Non-DAC | 0338-9543-05
UE1324D | 1000 | DAC | 0338-9543-06
UE1324DG | 1000 | DAC | 0338-9543-12

Exposure of pharmaceutical products to heat should be minimized. Avoid excessive heat. It is recommended the product be stored at room temperature (25°C/77°F); brief exposure up to 40°C/104°F does not adversely affect the product.

DIRECTIONS FOR USE OF VIAFLO PLASTIC CONTAINER

For Information on Risk of Air Embolism – see DOSAGE AND ADMINISTRATION.

To Open

Tear overwrap down side at slit and remove solution container. Visually inspect the container. If the outlet port protector is damaged, detached, or not present, discard container as solution path sterility may be impaired. Some opacity of the plastic due to moisture absorption during the sterilization process may be observed. This is normal and does not affect the solution quality or safety. The opacity will diminish gradually. Check for minute leaks by squeezing inner bag firmly. If leaks are found, discard solution as sterility may be impaired. If supplemental medication is desired, follow directions below.

1. Remove the container from the over wrap just before use.
2. Check for minute leaks by squeezing inner bag firmly. If leaks are found, discard solution, as sterility may be impaired.
3. Check solution for clarity and absence of foreign matter. If solution is not clear or contains foreign matter, discard the solution.

Preparation for Administration

1. Suspend container from eyelet support.
2. Remove plastic protector from outlet port at bottom of container.
  1. Grip the small wing on the neck of the port with one hand,
  2. grip the large wing on the cap with the other hand and twist,
  3. the cap will pop off.
3. Use an aseptic method to set up the infusion.
4. Attach administration set. Refer to directions accompanying set for connection, priming of the set and administration of the solution.

To Add Medication

Additives may be incompatible.

To add medication before solution administration

1. Prepare medication site.
2. Using syringe with 19 to 22 gauge needle, puncture resealable medication port and inject.
3. Mix solution and medication thoroughly. For high density medication such as potassium chloride, tap ports gently while ports are upright and mix thoroughly.

To add medication during solution administration

1. Close clamp on the set.
2. Prepare medication site.
3. Using syringe with 19 to 22 gauge needle, puncture resealable medication port and inject.
4. Remove container from IV pole and/or turn to an upright position.
5. Evacuate both ports by tapping them gently while container is in the upright position.
6. Mix solution and medication thoroughly.
7. Return container to in-use position and continue administration.

Baxter Healthcare Corporation
Deerfield, IL 60015 USA

Made in Spain

SA-30-02-879
Rev. November 2023

Baxter and Viaflo are trademarks of Baxter International Inc.

Customers can contact Baxter Medical Information at 1-800-933-0303 for more information on the containers.

PACKAGE/LABEL PRINCIPAL DISPLAY PANEL

Container Label

Baxter logo

NDC 0338-9543-01
UE1322

Viaflo logo

250 mL

0.9% Sodium Chloride Injection USP

pH 5.0 (4.5 – 7.0)
Osmolarity 308 mOsm/L (calc)

Sterile non pyrogenic
Single dose container

Each 100 mL contains 900 mg Sodium Chloride USP mEq/L
Sodium 154 Chloride 154

Additives may be incompatible Consult with pharmacist if available
when introducing additives Use aseptic technique Mix thoroughly
Do not store Dosage intravenously as directed by a physician
See directions Cautions Squeeze and inspect inner bags which
maintains product sterility Discard if leaks are found Must not be
used in series connections Do not use unless solution is clear

Rx Only Store unit in moisture barrier overwrap at room temperature
(25°C/77°F) until ready to use Avoid excessive heat See insert

VIAFLO is not made with natural rubber latex, DEHP, or PVC
Baxter Viaflo and PL-2442 are trademarks of Baxter
International Inc For product information
1-800-933-0303 Baxter Healthcare Corporation
Deerfield IL 60015 USA Made in Spain

BAR CODE
(01) 00303389543015

Lot
Expiry

UN-35-03-047

50
100
150
200

Container Label

Baxter Logo

NDC 0338-9657-75
UE1306G

Viaflo Logo
50 mL

0.9% Sodium Chloride Injection USP

pH 5.0 (4.5 – 7.0)
Sterile non pyrogenic
Osmolarity 308 mOsm/L (calc)
Single dose container

Each 50 mL contains 450 mg Sodium Chloride USP mEq/50mL
Sodium 8 Chloride 8

Read Package Leaflet for full Information

Additives may be incompatible Dosage intravenously
as directed by a physician Cautions Must not be
used in series connections Do not use unless solution
is clear Rx Only Store unit in moisture barrier
overwrap at room temperature (25°C/77°F) until ready
to use Avoid excessive heat See insert
VIAFLO is not made with natural rubber latex, DEHP,
or PVC

Baxter Viaflo and PL-2442 are trademarks of Baxter
International Inc

For product information 1-800-933-0303

07 Symbol

Baxter Healthcare Corporation
Deerfield IL 60015 USA Made in Spain

UN-35-04-346 1 Symbol

Lot Expiry

Barcode
(01)00303389657750

Container Label

Baxter Logo

NDC 0338-9659-75
UE1306DG

Viaflo Logo
50 mL

0.9% Sodium Chloride Injection USP

pH 5.0 (4.5 – 7.0)
Sterile non pyrogenic
Osmolarity 308 mOsm/L (calc)
Single dose container

Each 50 mL contains 450 mg Sodium Chloride USP mEq/50mL
Sodium 8 Chloride 8

Read Package Leaflet for full Information

Additives may be incompatible Dosage intravenously
as directed by a physician Cautions Must not be
used in series connections Do not use unless solution
is clear Rx Only Store unit in moisture barrier
overwrap at room temperature (25°C/77°F) until ready
to use Avoid excessive heat See insert
VIAFLO is not made with natural rubber latex, DEHP,
or PVC

Baxter Viaflo and PL-2442 are trademarks of Baxter
International Inc

For product information 1-800-933-0303

07 Symbol

Baxter Healthcare Corporation
Deerfield IL 60015 USA Made in Spain

UN-35-04-147 1 Symbol

Lot Expiry

Barcode
(01)00303389659754

Container Label

Baxter Logo

NDC 0338-9661-60
UE1307G

Viaflo Logo
100 mL

0.9% Sodium Chloride
Injection USP

pH 5.0 (4.5 – 7.0)
Sterile non pyrogenic
Osmolarity 308 mOsm/L (calc)
Single dose container

Each 100 mL contains 900 mg Sodium Chloride USP mEq/100mL
Sodium 15 Chloride 15

Read Package Leaflet for full Information

Additives may be incompatible Dosage intravenously
as directed by a physician Cautions Must not be
used in series connections Do not use unless solution
is clear Rx Only Store unit in moisture barrier
overwrap at room temperature (25°C/77°F) until ready
to use Avoid excessive heat See insert
VIAFLO is not made with natural rubber latex, DEHP,
or PVC

Baxter Viaflo and PL-2442 are trademarks of Baxter
International Inc

For product information 1-800-933-0303

07 Symbol

Baxter Healthcare Corporation
Deerfield IL 60015 USA Made in Spain

UN-35-04-347 1 Symbol

Lot Expiry

Barcode
(01)00303389661603

Container Label

Baxter Logo

NDC 0338-9663-60
UE1307DG

Viaflo Logo
100 mL

0.9% Sodium Chloride
Injection USP

pH 5.0 (4.5 – 7.0)
Sterile non pyrogenic
Osmolarity 308 mOsm/L (calc)
Single dose container

Each 100 mL contains 900 mg Sodium Chloride USP mEq/100mL
Sodium 15 Chloride 15

Read Package Leaflet for full Information

Additives may be incompatible Dosage intravenously
as directed by a physician Cautions Must not be
used in series connections Do not use unless solution
is clear Rx Only Store unit in moisture barrier
overwrap at room temperature (25°C/77°F) until ready
to use Avoid excessive heat See insert
VIAFLO is not made with natural rubber latex, DEHP,
or PVC

Baxter Viaflo and PL-2442 are trademarks of Baxter
International Inc

For product information 1-800-933-0303

07 Symbol

Baxter Healthcare Corporation
Deerfield IL 60015 USA Made in Spain

UN-35-04-148 1 Symbol

Lot Expiry

Barcode
(01)00303389663607

Carton Label

UE1306G 75 x 50 mL (≈ 6 kg)

0.9% Sodium Chloride
Injection, USP

Formula per 50 mL
Sodium Chloride 450 mg
Water for Injection
Osmolarity 308 m0sm/L (calc)
mmol per 50 mL (approx..)
Sodium 8
Chloride 8
pH 5.0 (4.5 – 7.0)

IV administration.
Read package insert before use.
Keep out of the reach and sight of children.
Do not connect partially used drugs.

Baxter Healthcare Corporation
Deerfield IL 60015 USA

Made in Spain

Viaflo Logo

Lot: ????????
Exp: YYYY/MM

P333E744
?? – 00001

Barcode
(01)50303389657755(17)YYMMOO(10)????????

UE1306G 75 x 50 mL (≈ 6 kg)

0.9% Sodium
Chloride
Injection, USP

Viaflo Logo

2D barcode

Lot:
????????
Exp:
YYYY/MM

(01)50303389657755(17)YYMMOO(10)????????

Carton Label

UE1306DG 75 x 50 mL (≈ 6 kg)

0.9% Sodium Chloride
Injection, USP

Formula per 50 mL
Sodium Chloride 450 mg
Water for Injection
Osmolarity 308 m0sm/L (calc)
mmol per 50 mL (approx..)
Sodium 8
Chloride 8
pH 5.0 (4.5 – 7.0)

IV administration.
Read package insert before use.
Keep out of the reach and sight of children.
Do not connect partially used drugs.

Baxter Healthcare Corporation
Deerfield IL 60015 USA

Made in Spain

Viaflo Logo

Lot: ????????
Exp: YYYY/MM

P333E748
?? – 00001

Barcode
(01)50303389659759(17)YYMMOO(10)????????

UE1306DG
75 x 50 mL (≈ 6 kg)

0.9% Sodium
Chloride
Injection, USP

Viaflo Logo

2D barcode

Lot:
????????
Exp:
YYYY/MM

(01)50303389659759(17)YYMMOO(10)????????

Carton Label

UE1307G 60 x 100 mL (≈ 8 kg)

0.9% Sodium Chloride
Injection, USP

Formula per 100 mL
Sodium Chloride 900 mg
Water for Injection
Osmolarity 308 m0sm/L (calc)
mmol per 100 mL (approx..)
Sodium 15
Chloride 15
pH 5.0 (4.5 – 7.0)

IV administration.
Read package insert before use.
Keep out of the reach and sight of children.
Do not connect partially used drugs.

Baxter Healthcare Corporation
Deerfield IL 60015 USA

Made in Spain

Viaflo Logo

Lot: ????????
Exp: YYYY/MM

P333E745
?? – 00001

Barcode
(01)503033896616608(17)YYMMOO(10)????????

UE1307G
60 x 100 mL (≈ 8 kg)

0.9% Sodium
Chloride
Injection, USP

Viaflo Logo

2D barcode

Lot:
????????
Exp:
YYYY/MM

(01)5030338966616608(17)YYMMOO(10)????????

Carton Label

UE1307DG 60 x 100 mL (≈ 8 kg)

0.9% Sodium Chloride
Injection, USP

Formula per 100 mL
Sodium Chloride 900 mg
Water for Injection
Osmolarity 308 m0sm/L (calc)
mmol per 100 mL (approx..)
Sodium 15
Chloride 15
pH 5.0 (4.5 – 7.0)

IV administration.
Read package insert before use.
Keep out of the reach and sight of children.
Do not connect partially used drugs.

Baxter Healthcare Corporation
Deerfield IL 60015 USA

Made in Spain

Viaflo Logo

Lot: ????????
Exp: YYYY/MM

P333E749
?? – 00001

Barcode
(01)50303389663602(17)YYMMOO(10)????????

UE1307G
60 x 100 mL (≈ 8 kg)

0.9% Sodium
Chloride
Injection, USP

Viaflo Logo

2D barcode

Lot:
????????
Exp:
YYYY/MM

(01)50303389663602(17)YYMMOO(10)????????